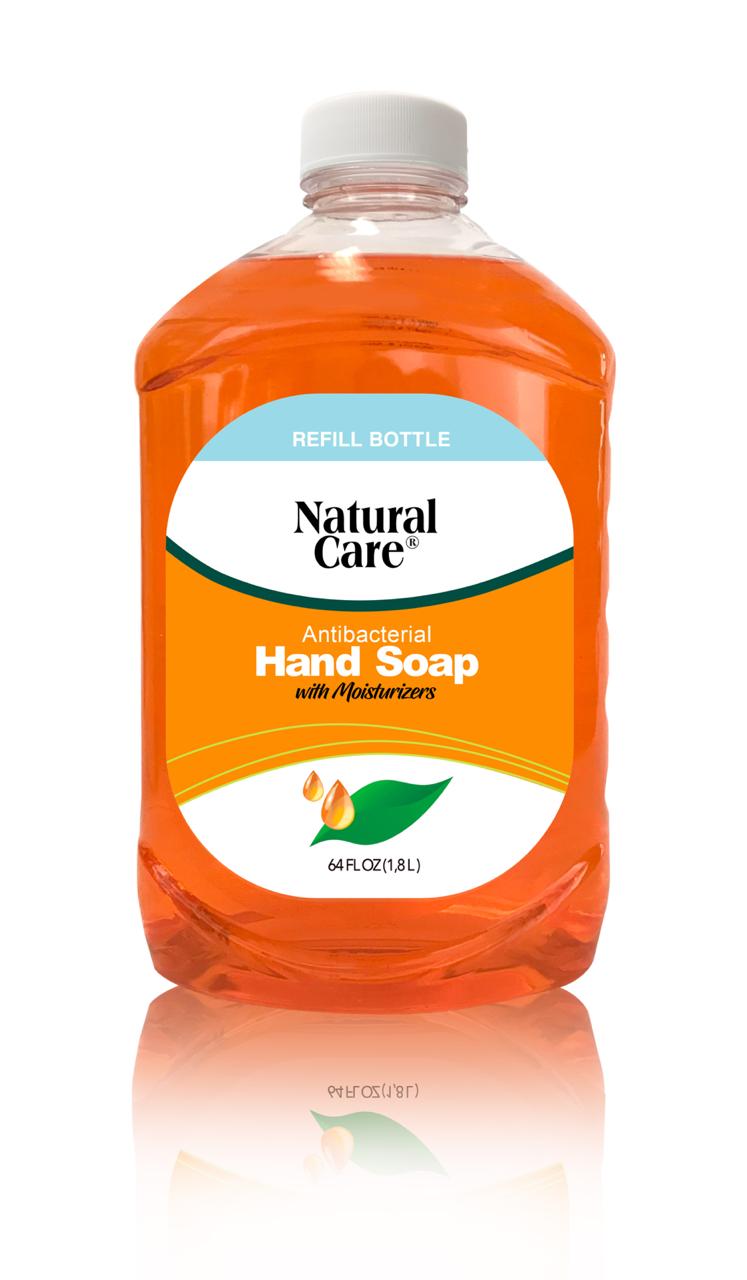 DRUG LABEL: NATURAL
NDC: 78440-001 | Form: GEL
Manufacturer: INTERNATIONAL GENERAL TRADING CORP
Category: otc | Type: HUMAN OTC DRUG LABEL
Date: 20200713

ACTIVE INGREDIENTS: BENZALKONIUM CHLORIDE 1.3 g/1 mL
INACTIVE INGREDIENTS: WATER

NATURAL CARE ANTIBACTERIAL

This is a hand sanitizer manufactured according to the Temporary Policy for Preparation of Certain Alcohol-Based Hand Sanitizer Products During the Public Health Emergency (CoViD-19); Guidance for Industry.

The hand sanitizer is manufactured using only the following United States Pharmacopoeia (USP) grade ingredients in the preparation of the product (percentage in final product formulation) consistent with World Health Organization (WHO) recommendations:

1. Alcohol (ethanol) (USP or Food Chemical Codex (FCC) grade) (80%, volume/volume (v/v)) in an aqueous solution denatured according to Alcohol and Tobacco Tax and Trade Bureau regulations in 27 CFR part 20.
2. Glycerol (1.45% v/v).
3. Hydrogen peroxide (0.125% v/v).
4. Sterile distilled water or boiled cold water.

The firm does not add other active or inactive ingredients. Different or additional ingredients may impact the quality and potency of the product.

Active Ingredient(s)

BENZALKONIUM CHLORIDE

Purpose

Antibacterial

Use

FOR HANDWASHING TO DECREASE BATERIA ON THE SKIN

Warnings

For external use only.

Do not use

- in children less than 2 months of age
- on open skin wounds

When using this product do not get into yes. If contact occurs rinse eye throughly with water

stop use and ask a docor if irritation or redness develops

Keep out of reach of children. If swallowed, get medical help or contact a Poison Control Center right away.

Directions

Wash hands, apply palful to hhand rub thoughly and rinse

Other information

- Store between 15-30C (59-86F)
- Avoid freezing and excessive heat above 40C (104F)

Inactive ingredients

WATER, SODIUM LAURYLETHER SULFATHEM COCOAMIDO PROPYL, BETAINE, GLYCERIN, ESSENTIAL OILS, SODIUM CHORIDE, COLLAGEN. SODIUMFEINT, SALT, ALOE VERA, YELLOW#5 d&c, RED#4 D&C